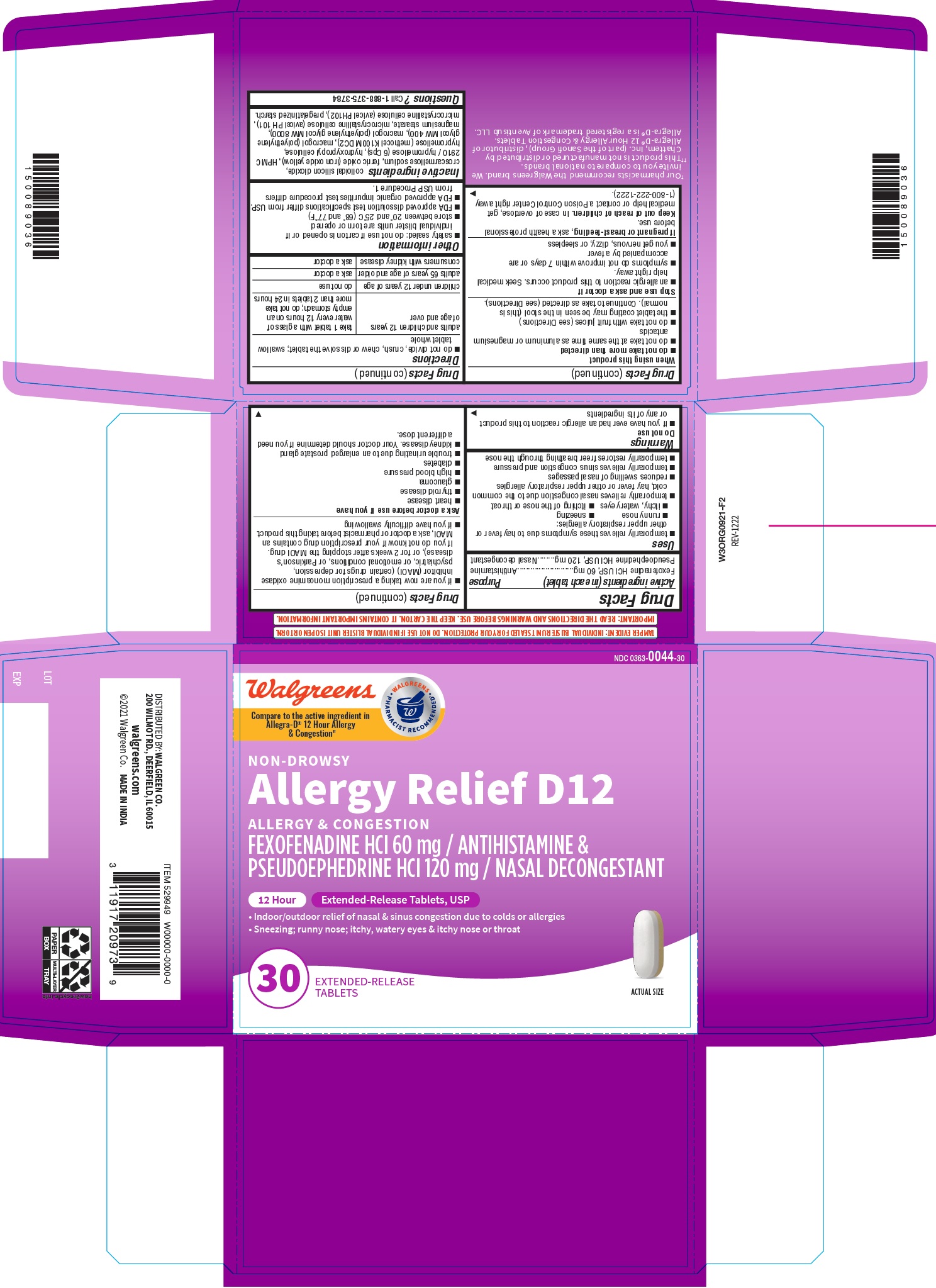 DRUG LABEL: Fexofenadine Hydrochloride and Pseudoephedrine Hydrochloride
NDC: 0363-0044 | Form: TABLET, EXTENDED RELEASE
Manufacturer: Walgreens Company
Category: otc | Type: HUMAN OTC DRUG LABEL
Date: 20251210

ACTIVE INGREDIENTS: FEXOFENADINE HYDROCHLORIDE 60 mg/1 1; PSEUDOEPHEDRINE HYDROCHLORIDE 120 mg/1 1
INACTIVE INGREDIENTS: MICROCRYSTALLINE CELLULOSE 101; Croscarmellose Sodium; Ferric Oxide Yellow; Silicon Dioxide; Magnesium Stearate; Polyethylene Glycol 400; Hypromellose 2208 (100000 Mpa.S); HYDROXYPROPYL CELLULOSE (45000 WAMW); Hypromellose 2910 (6 Mpa.S); Polyethylene Glycol 8000; Starch, Corn; MICROCRYSTALLINE CELLULOSE 102

Fexofenadine Hydrochloride and Pseudoephedrine Hydrochloride Extended-Release Tablets USP, 60 mg/120 mg

Active ingredient(s)

Fexofenadine HCl USP, 60 mg

Pseudoephedrine HCl USP, 120 mg

Purpose

Antihistamine

Nasal decongestant

Use(s)

- temporarily relieves these symptoms due to hay fever or other upper respiratory allergies:
- runny nose
- sneezing
- itchy, watery eyes
- itching of the nose or throat
- temporarily relives nasal congestion due to the common cold, hay fever or other upper respiratory allergies
- reduces swelling of nasal passages
- temporarily relieves sinus congestion and pressure
- temporarily restores freer breathing through the nose

Warnings

Do not use

- if you have ever had an allergic reaction to this product or any of its ingredients
- if you are now taking a prescription monoamine oxidase inhibitor (MAOI) (certain drugs for depression, psychiatric, or emotional conditions, or Parkinson’s disease), or for 2 weeks after stopping the MAOI drug. If you do not know if your prescription drug contains an MAOI, ask a doctor or pharmacist before taking this product.
- if you have difficulty swallowing

Ask a doctor before use if you have

- heart disease
- thyroid disease
- glaucoma
- high blood pressure
- diabetes
- trouble urinating due to an enlarged prostate gland
- kidney disease. Your doctor should determine if you need a different dose.

When using this product

- do not take more than directed
- do not take at the same time as aluminum or magnesium antacids
- do not take with fruit juices (see Directions)
- the tablet coating may be seen in the stool (this is normal). Continue to take as directed (see Directions).

Stop use and ask doctor if

- an allergic reaction to this product occurs. Seek medical help right away.
- symptoms do not improve within 7 days or are accompanied by a fever
- you get nervous, dizzy, or sleepless

If pregnant or breast-feeding

ask a health professional before use.

Keep out of reach of children

In case of overdose, get medical help or contact a Poison Control Center right away.

Directions

- do not divide, crush, chew or dissolve the tablet; swallow tablet whole

adults and children 12 years of age and over | take 1 tablet with a glass of water every 12 hours on an empty stomach; do not take more than 2 tablets in 24 hours
children under 12 years of age | do not use
adults 65 years of age and older | ask a doctor
consumers with kidney disease | ask a doctor

Other information

- safety sealed: do not use if carton is opened or if individual blister units are torn or opened
- store between 20° to 25°C (68° to 77°F) store between 20° to 25°C (68° to 77°F)
- FDA approved dissolution test specifications differ from USP.
- FDA approved organic impurities test procedure differs from USP Procedure 1.

Inactive ingredients

colloidal silicon dioxide, croscarmellose sodium, ferric oxide (iron oxide yellow), HPMC 2910 / hypromellose (6 Cps), hydroxypropyl cellulose, hypromellose (methocel K100M DC2), macrogol (polyethylene glycol MW 400), macrogol (polyethylene glycol MW 8000), magnesium stearate, microcrystalline cellulose (avicel PH 101), microcrystalline cellulose (avicel PH102), pregelatinized starch.

Questions?

Call 1-888-375-3784